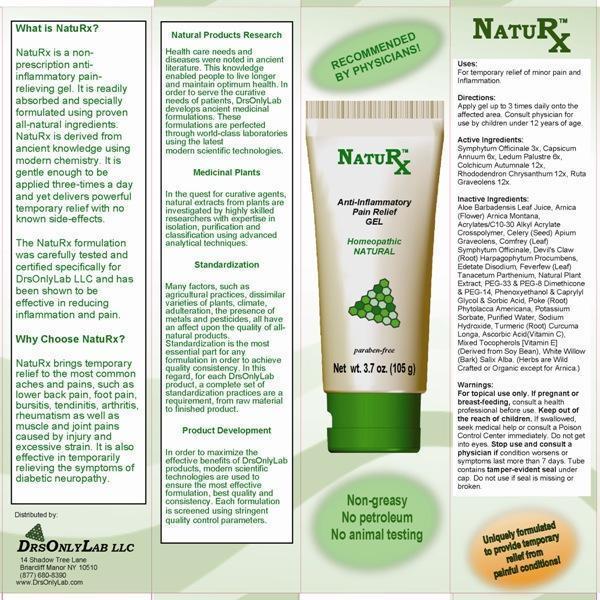 DRUG LABEL: NatuRx
NDC: 53723-0001 | Form: GEL
Manufacturer: DrsOnlyLab LLC
Category: homeopathic | Type: HUMAN OTC DRUG LABEL
Date: 20130422

ACTIVE INGREDIENTS: COMFREY ROOT 3 [hp_X]/1 g; CAPSICUM 6 [hp_X]/1 g; LEDUM PALUSTRE TWIG 6 [hp_X]/1 g; COLCHICUM AUTUMNALE BULB 12 [hp_X]/1 g; RHODODENDRON AUREUM LEAF 12 [hp_X]/1 g; RUTA GRAVEOLENS FLOWERING TOP 12 [hp_X]/1 g
INACTIVE INGREDIENTS: ALOE VERA LEAF; ARNICA MONTANA FLOWER; CARBOMER INTERPOLYMER TYPE A (ALLYL SUCROSE CROSSLINKED); CELERY SEED; COMFREY LEAF; HARPAGOPHYTUM PROCUMBENS ROOT; EDETATE DISODIUM; FEVERFEW; OREGANO; POLYETHYLENE GLYCOL 1500; PEG-8 DIMETHICONE; POLYETHYLENE GLYCOL 700; PHENOXYETHANOL; CAPRYLYL GLYCOL; SORBIC ACID; PHYTOLACCA AMERICANA ROOT; POTASSIUM SORBATE; WATER; SODIUM HYDROXIDE; TURMERIC; ASCORBIC ACID; TOCOPHEROL; SALIX ALBA BARK

Drug Facts

ACTIVE INGREDIENTS

Symphytum Officinale 3X, Capsicum Annuum 6X, Ledum Palustre 6X, Colchicum Autumnale 12X, Rhododendron Chrysanthum 12X, Ruta Graveolens 12X

INDICATIONS

For temporary relief of minor pain and inflammation.

WARNINGS

For topical use only. If pregnant or breast-feeding, consult a health professional before use. Keep out of the reach of children. If swallowed, seek medical help or consult a Poison Control Center immediately. Do not get into eyes. Stop use and consult a physician if condition worsens or symptoms last more than 7 days. Tube contains tamper-evident seal under cap. Do not use if seal is missing or broken.

DIRECTIONS

Apply gel up to 3 times daily onto the affected area. Consult physician for use by children under 12 years of age.

INACTIVE INGREDIENTS

Aloe Barbadensis Leaf Juice, Arnica Montana (Flower), Acrylates C10-30 Alkyl Acrylate Crosspolymer, Celery (seed), Comfrey (leaf), Devil's Claw (root), Edetate Disodium, Feverfew (leaf), Natural plant extract, PEG-33, PEG-8 Dimethicone, PEG-14, Phenoxyethanol, Caprylyl Glycol, Sorbic Acid, Poke (root), Potassium sorbate, Purified Water, Sodium Hydroxide, Tumeric (root), Ascorbic Acid, Mixed Tocopherols, Salix Alba (bark)

KEEP OUT OF REACH OF CHILDREN

If swallowed, seek medical help or consult a Poison Control Center immediately.

INDICATIONS AND USAGE

For temporary relief of minor pain and inflammation.

QUESTIONS

DRSONLYLAB LLC

14 Shadow Tree Lane

Briarcliff Manor, NY 10510

(877) 680-8390

www.DrsOnlyLab.com

PACKAGE LABEL

NATURX

Anti-Inflammatory

Pain Relief

GEL

Homeopathic

NATURAL

paraben-free

Net wt. 3.7 oz. (105 g)